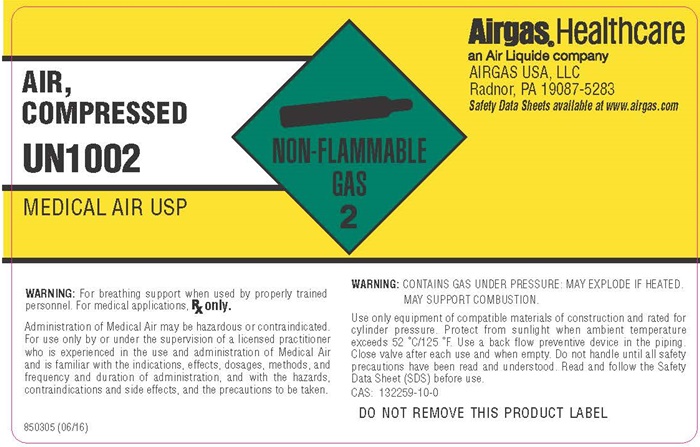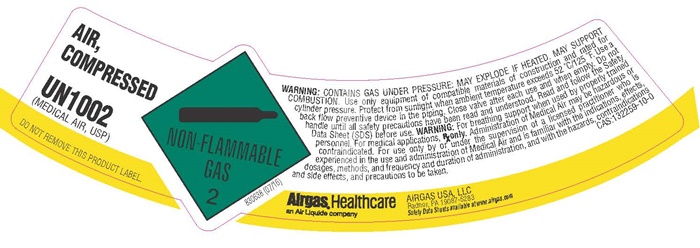 DRUG LABEL: Air
NDC: 11054-110 | Form: GAS
Manufacturer: AIRGAS USA, LLC
Category: prescription | Type: HUMAN PRESCRIPTION DRUG LABEL
Date: 20250903

ACTIVE INGREDIENTS: Oxygen 210 mL/1 L
INACTIVE INGREDIENTS: Nitrogen 790 mL/1 L

Air, USP (Medical Air) - 110

Medical Air SL product label

AIR,
COMPRESSED

UN 1002

(MEDICAL AIR, USP)

DO NOT REMOVE THIS PRODUCT LABEL

NON-FLAMMABLE GAS 2

830638 (07/16)

WARNING: CONTAINS GAS UNDER PRESSURE: MAY EXPLODE IF HEATED. MAY SUPPORT COMBUSTION. Use only with equipment of compatible materials of construction and rated for cylinder pressure. Protect from sunlight when ambient temperature exceeds 52°C/125°F. Use a back flow preventive device in the piping. Close valve after each use and when empty. Do not handle until all safety precautions have been read and understood. Read and follow the Safety Data Sheet (SDS) before use.

WARNING: For breathing support when used by properly trained personnel. For medical applications, Rx only. Administration of Medical Air may be hazardous or contraindicated. For use only by or under the supervision of a licensed practitioner who is experienced in the use and administration of Medical Air and is familiar with the indications, effects, dosages, methods, and frequency and duration of administration and with the hazards, contraindications and side effects, and the precautions to be taken.

CAS: 132259-10-0

Airgas Healthcare®
an Air Liquide company
AIRGAS USA, LLC
Radnor, PA 19087-5283

Safety Data Sheets available at www.airgas.com

Medical Air product label

AIR,
COMPRESSED

UN 1002

MEDICAL AIR, USP

DO NOT REMOVE THIS PRODUCT LABEL

NON-FLAMMABLE GAS 2

WARNING: For breathing support when used by properly trained personnel. For medical applications, Rx only.

Administration of Medical Air may be hazardous or contraindicated. For use only by or under the supervision of a licensed practitioner who is experienced in the use and administration of Medical Air and is familiar with the indications, effects, dosages, methods, and frequency and duration of administration and with the hazards, contraindications and side effects, and the precautions to be taken.

WARNING: CONTAINS GAS UNDER PRESSURE: MAY EXPLODE IF HEATED. MAY SUPPORT COMBUSTION.

Use only with equipment of compatible materials of construction and rated for cylinder pressure. Protect from sunlight when ambient temperature exceeds 52°C/125°F. Use a back flow preventive device in the piping. Close valve after each use and when empty. Do not handle until all safety precautions have been read and understood. Read and follow the Safety Data Sheet (SDS) before use.

CAS: 132259-10-0

DO NOT REMOVE THIS PRODUCT LABEL

Airgas Healthcare®
an Air Liquide company
AIRGAS USA, LLC
Radnor, PA 19087-5283

Safety Data Sheets available at www.airgas.com

850305 (06/16)